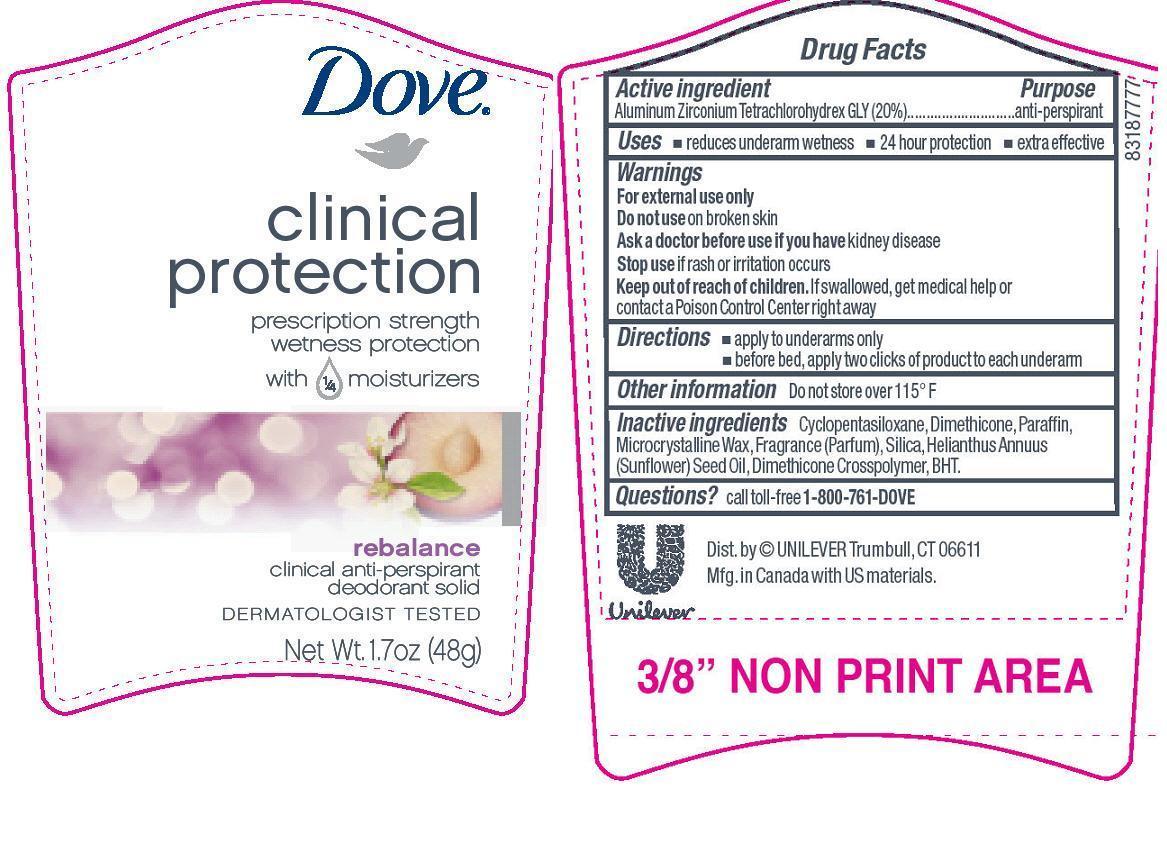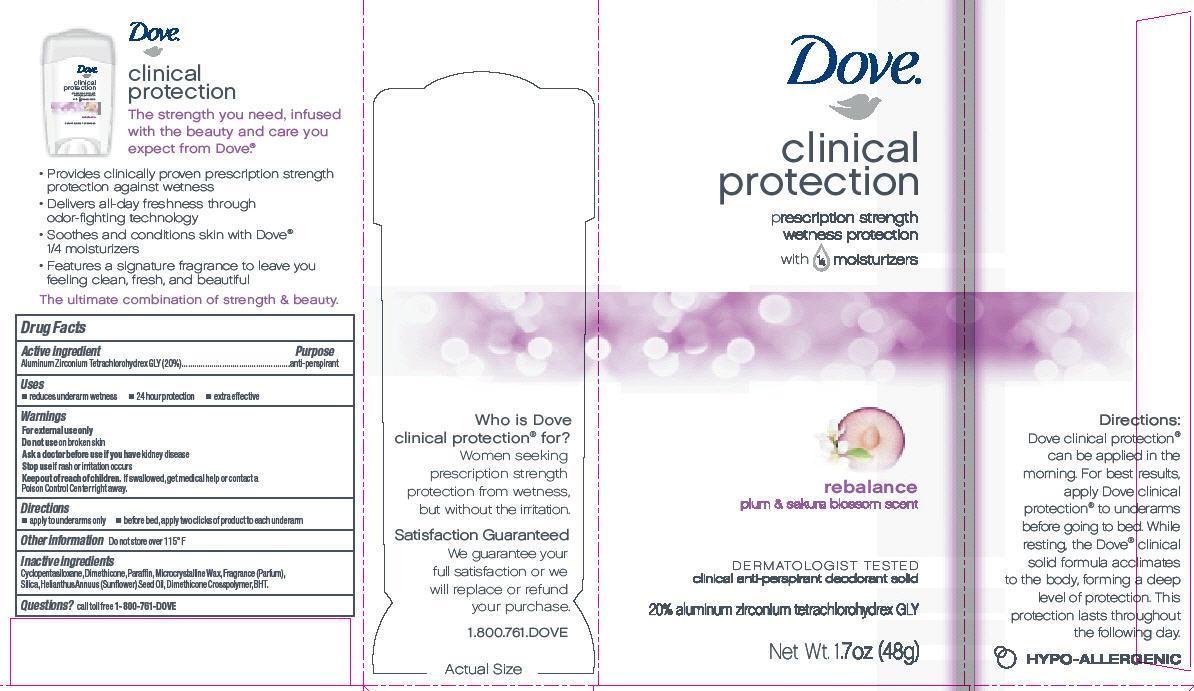 DRUG LABEL: Dove
NDC: 64942-1140 | Form: STICK
Manufacturer: Conopco Inc. d/b/a Unilever
Category: otc | Type: HUMAN OTC DRUG LABEL
Date: 20131022

ACTIVE INGREDIENTS: Aluminum Zirconium Tetrachlorohydrex GLY 20 g/100 g
INACTIVE INGREDIENTS: CYCLOMETHICONE 5; DIMETHICONE; PARAFFIN; SILICON DIOXIDE; SUNFLOWER OIL; BUTYLATED HYDROXYTOLUENE; MICROCRYSTALLINE WAX

Dove Clinical Protection Rebalance antiperspirant deodorant

Active Ingredient

Aluminum Zirconium Tetrachlorohydrex GLY (20%)

Purpose
anti-perspirant

Warnings
For external use only

Do not use on broken skin

Ask a doctor before use if you have kidney disease

Stop use if rash or irritation occurs

Keep out of reach of children. If swallowed, get medical help or contact a Poison Control Center right away.

Uses
▪ reduces underarm wetness
▪ 24 hour protection
▪ extra effective

Directions
▪ apply to underarms only
▪ before bed, apply two clicks of product to each underarm

Inactive ingredients
Cyclopentasiloxane
Dimethicone
Paraffin
Microcrystalline wax
Fragrance (Parfum)
Silica
Helianthus Annuus (Sunflower) Seed Oil
Dimethicone Crosspolymer
BHT

Questions? Call toll-free 1-800-761-DOVE